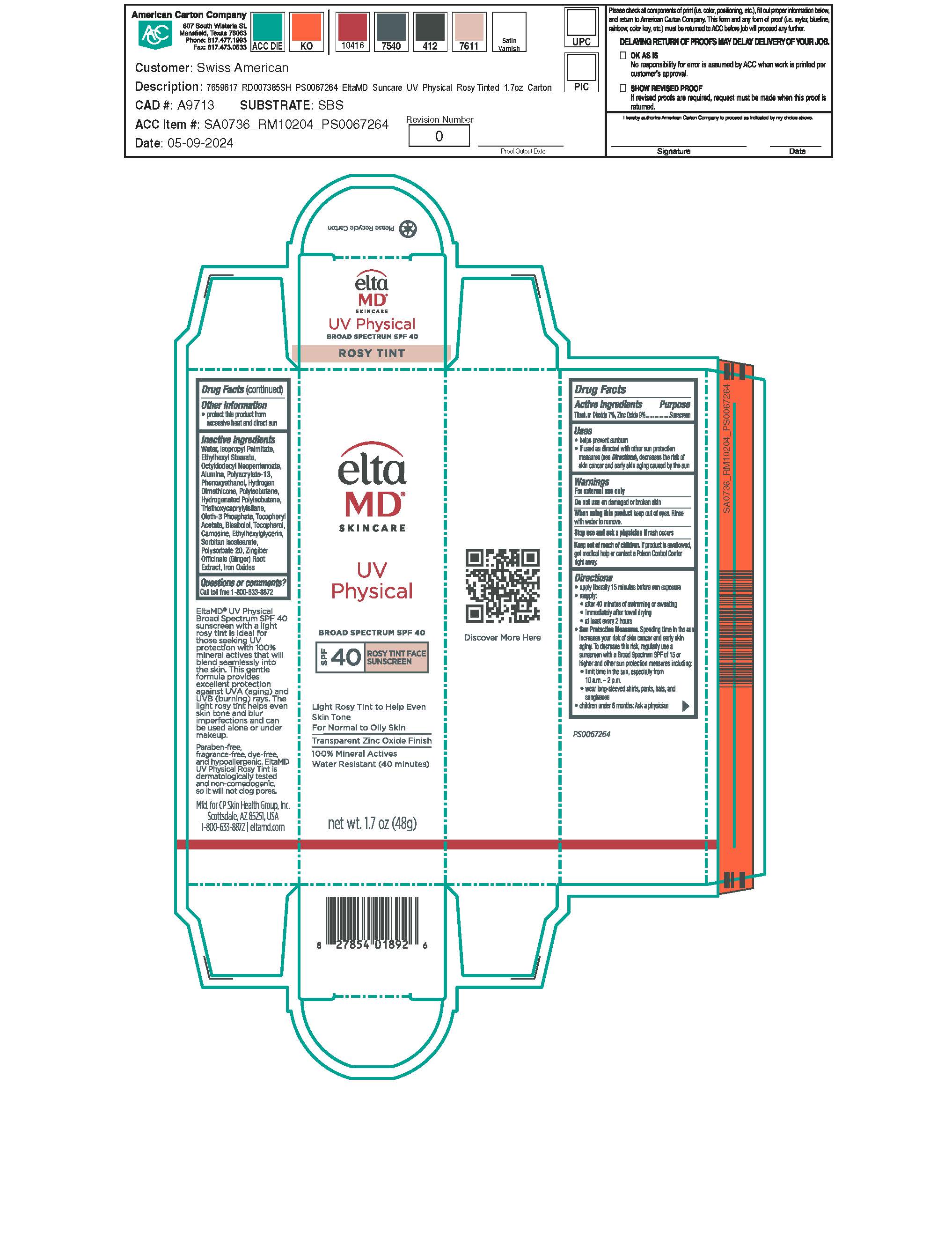 DRUG LABEL: EltaMD UV Physical Rosy Tint SPF40
NDC: 72043-2257 | Form: LOTION
Manufacturer: CP Skin Health Group, Inc
Category: otc | Type: HUMAN OTC DRUG LABEL
Date: 20240905

ACTIVE INGREDIENTS: TITANIUM DIOXIDE 70 g/1000 g; ZINC OXIDE 90 g/1000 g
INACTIVE INGREDIENTS: WATER; ISOPROPYL PALMITATE; ETHYLHEXYL STEARATE; OCTYLDODECYL NEOPENTANOATE; POLYACRYLATE-13; PHENOXYETHANOL; HYDROGENATED POLYISOBUTENE (450 MW); TRIETHOXYCAPRYLYLSILANE; OLETH-3 PHOSPHATE; CITRIC ACID MONOHYDRATE; TOCOPHEROL; ETHYLHEXYLGLYCERIN; CARNOSINE; POLYSORBATE 20; SODIUM HYDROXIDE; PHOSPHORIC ACID; CANOLA OIL; ZINGIBER OFFICINALE WHOLE; ALUMINUM OXIDE; .ALPHA.-TOCOPHEROL ACETATE; LEVOMENOL; FERRIC OXIDE YELLOW; FERROSOFERRIC OXIDE; FERRIC OXIDE RED; HYDROGEN DIMETHICONE (13 CST); POLYISOBUTYLENE (45000 MW)

EltaMD UV Physical Rosy Tint SPF40

Warnings

For external use only. Do not use on damaged or broken skin. When using this product keep out of eyes. Rinse with water to remove. Stop use and ask a physician if rash occurs. If product is swallowed get medical help or contact a Poison Control Center right away.

Active Ingredients

Titanium Dioxide 7.0%

Zinc Oxide 9.0%

Purpose

Sunscreen

Indications & Uses:

Helps prevent sunburn. If used as directed with other sun protection measure (See Directions), decreases the risk of skin cancer and early skin aging caused by the sun.

Directions

Apply liberally 15 minutes before sun exposure. Reapply: after 40 minutes of swimming or sweating, immediately after towel drying and at least every 2 hours. Sun Protection Measures: Spending time in the sun increases your risk of skin cancer and early skin aging. To decrease this risk, regularly use a sunscreen with a broad-spectrum SPF of 15 or higher and other sun protection measures including: limit time in the sun, especially from 10 am to 2 pm. Wear long-sleeve shirts, pants, hats, and sunglasses. Children under 6 months: ask a physician.

Keep out of reach of children

Other Information

Protect this product from excessive heat and direct sun.

Inactive ingredients

water, isopropyl plamitate, ethylhexyl stearate, octyldodecyl neopentanoate, alumina, polyacrylate-13, phenoxyethanol, hydrogen dimethicone, polyisobutene, triethoxycaprylylsilane, oleth-3 phosphate, citric acid, tocopheryl acetate, bisabolol, tocopherol, ethylhexylglycerin, carnosine, polysorbate 20, sodium hydroxide, phosphoric acid, canola oil, zingiber officinale (ginger) root extract, iron oxides

Questions?

Call 1-800-633-8872

visit www.eltamd.com